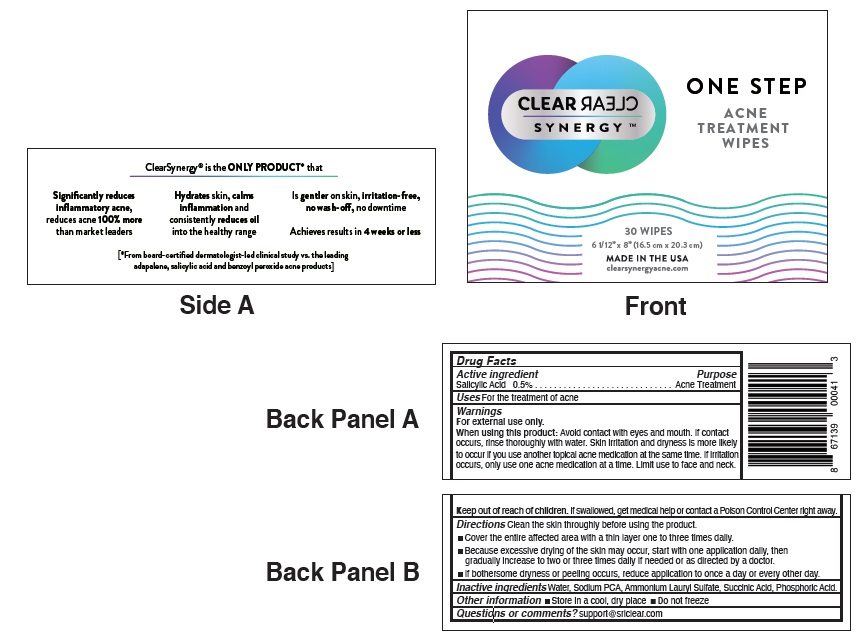 DRUG LABEL: ClearSynergy
NDC: 71617-102 | Form: CLOTH
Manufacturer: SRL Enterprises, LLC
Category: otc | Type: HUMAN OTC DRUG LABEL
Date: 20241008

ACTIVE INGREDIENTS: SALICYLIC ACID 5 mg/1 mL
INACTIVE INGREDIENTS: WATER; SODIUM PYRROLIDONE CARBOXYLATE; AMMONIUM LAURYL SULFATE; SUCCINIC ACID; PHOSPHORIC ACID

Active Ingredient

Salicylic Acid 0.5%

Purpose

Acne Treatment

Uses

For the treatment of acne.

Warnings

For external use only.

When using this product:Avoid contact with eyes and mouth. If contact occurs, rinse thoroughly with water. Skin irritation and dryness is more likely to occur if you use another topical acne medication at the same time. If irritation occurs, only use one acne medication at a time. Limit use to face and neck.

Keep out of reach of children.If swallowed, get medical help or contact a Poison Control Center right away.

Directions

- Cover the entire affected area with a thin layer one to three times daily.
- Because excessive drying of the skin may occur, start with one application daily, then gradually increase to two or three times daily if needed or as directed by a doctor.
- If bothersome dryness or peeling occurs, reduce application to once a day or every other day.

Inactive ingredients

Water, Sodium PCA, Ammonium Lauryl Sulfate, Succinic Acid, Phosphoric Acid.

STORAGE AND HANDLING

- Store in a cool, dry place
- Do not freeze

Questions or comments?support@srlclear.com